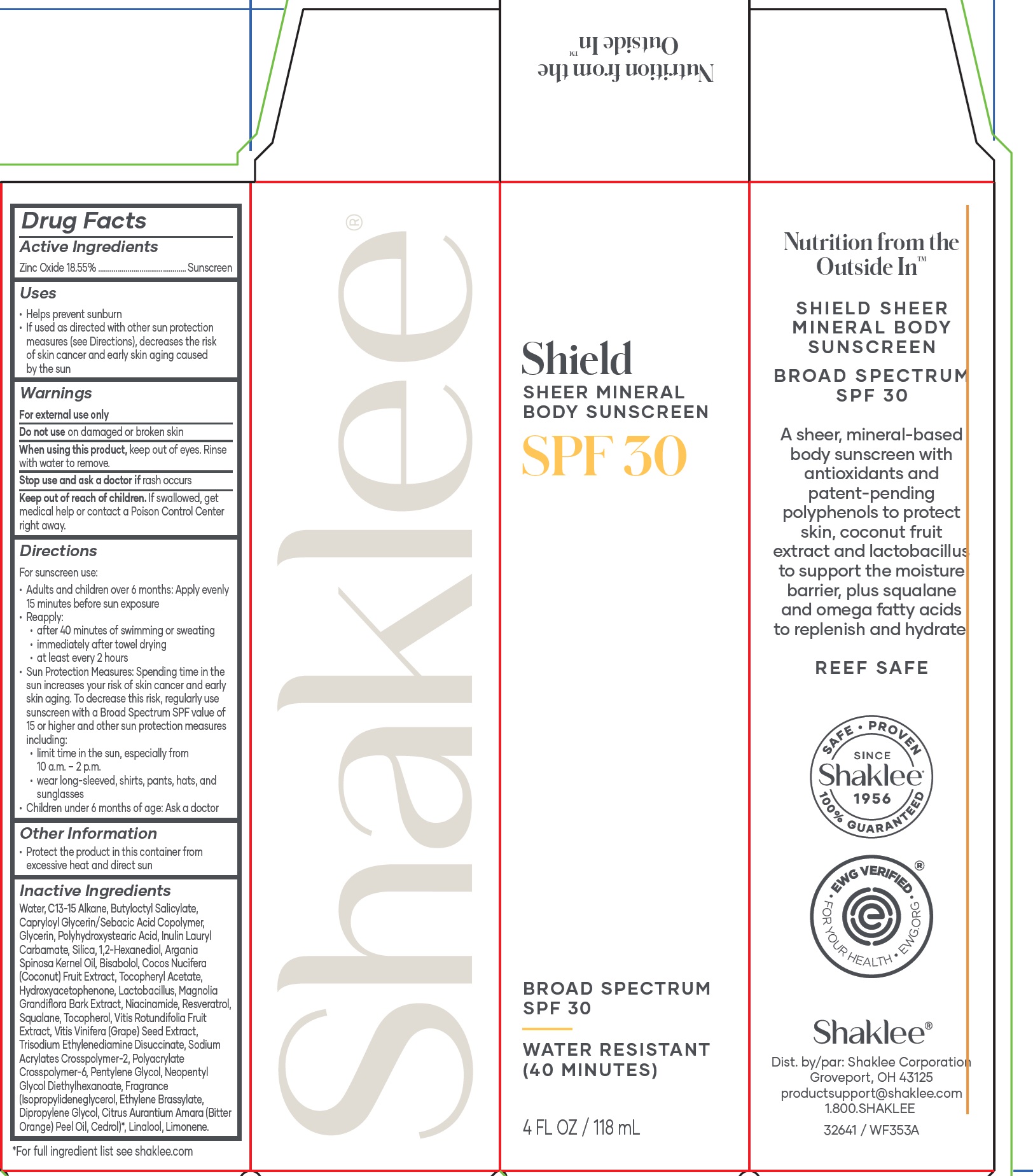 DRUG LABEL: Shaklee Shield Sheer Mineral Body Sunscreen SPF 30
NDC: 59899-024 | Form: LOTION
Manufacturer: Shaklee Corp
Category: otc | Type: HUMAN OTC DRUG LABEL
Date: 20250731

ACTIVE INGREDIENTS: ZINC OXIDE 185.5 mg/1 mL
INACTIVE INGREDIENTS: WATER; C13-15 ALKANE; BUTYLOCTYL SALICYLATE; GLYCERIN; INULIN LAURYL CARBAMATE; SILICON DIOXIDE; 1,2-HEXANEDIOL; ARGAN OIL; LEVOMENOL; COCONUT; .ALPHA.-TOCOPHEROL ACETATE; HYDROXYACETOPHENONE; BIFIDOBACTERIUM ANIMALIS LACTIS; MAGNOLIA GRANDIFLORA BARK; NIACINAMIDE; RESVERATROL; SQUALANE; TOCOPHEROL; VITIS VINIFERA SEED PROANTHOCYANIDINS; TRISODIUM ETHYLENEDIAMINE DISUCCINATE; SODIUM ACRYLATES CROSSPOLYMER-2; AMMONIUM ACRYLOYLDIMETHYLTAURATE, DIMETHYLACRYLAMIDE, LAURYL METHACRYLATE AND LAURETH-4 METHACRYLATE COPOLYMER, TRIMETHYLOLPROPANE TRIACRYLATE CROSSLINKED (45000 MPA.S); PENTYLENE GLYCOL; NEOPENTYL GLYCOL DIETHYLHEXANOATE; SOLKETAL; ETHYLENE BRASSYLATE; DIPROPYLENE GLYCOL; BITTER ORANGE OIL; LINALOOL, (+/-)-; LIMONENE, (+)-

Shaklee Shield Sheer Mineral Body Sunscreen SPF 30

Active Ingredients

Zinc Oxide 18.55%

PURPOSE

Sunscreen

Uses

• Helps prevent sunburn
• If used as directed with other sun protection measures (see Directions), decreases the risk of skin cancer and early skin aging caused by the sun

Warnings

For external use only

Do not use

on damaged or broken skin

When using this product,

keep out of eyes. Rinse with water to remove.

Stop use and ask a doctor if

rash occurs

Keep out of reach of children.

If swallowed, get medical help or contact a Poison Control Center right away.

Directions

For sunscreen use:
• Adults and children over 6 months: Apply evenly 15 minutes before sun exposure
• Reapply:
• after 40 minutes of swimming or sweating
• immediately after towel drying
• at least every 2 hours
• Sun Protection Measures: Spending time in the sun increases your risk of skin cancer and early skin aging. To decrease this risk, regularly use sunscreen with a Broad Spectrum SPF value of 15 or higher and other sun protection measures including:
• limit time in the sun, especially from 10 a.m. – 2 p.m.
• wear long-sleeved, shirts, pants, hats, and sunglasses
• Children under 6 months of age: Ask a doctor

Other Information

• Protect the product in this container from excessive heat and direct sun

Inactive Ingredients

Water, C13-15 Alkane, Butyloctyl Salicylate, Capryloyl Glycerin/Sebacic Acid Copolymer, Glycerin, Polyhydroxystearic Acid, Inulin Lauryl Carbamate, Silica, 1,2-Hexanediol, Argania Spinosa Kernel Oil, Bisabolol, Cocos Nucifera (Coconut) Fruit Extract, Tocopherol Acetate, Hydroxyacetophenone, Lactobacillus, Magnolia Grandiflora Bark Extract, Niacinamide, Resveratrol, Squalane, Tocopherol, Vitis Rotundifolia Fruit Extract, Vitis Vinifera (Grape) Seed Extract, Trisodium Ethylenediamine Disuccinate, Sodium Acrylates Crosspolymer-2, Polyacrylate Crosspolymer-6, Pentylene Glycol, Neopentyl Glycol Diethylhexanoate, Fragrance (Isopropylideneglycerol, Ethylene Brassylate, Dipropylene Glycol, Citrus Aurantium Amara (Bitter Orange) Peel Oil), Linalool, Limonene.